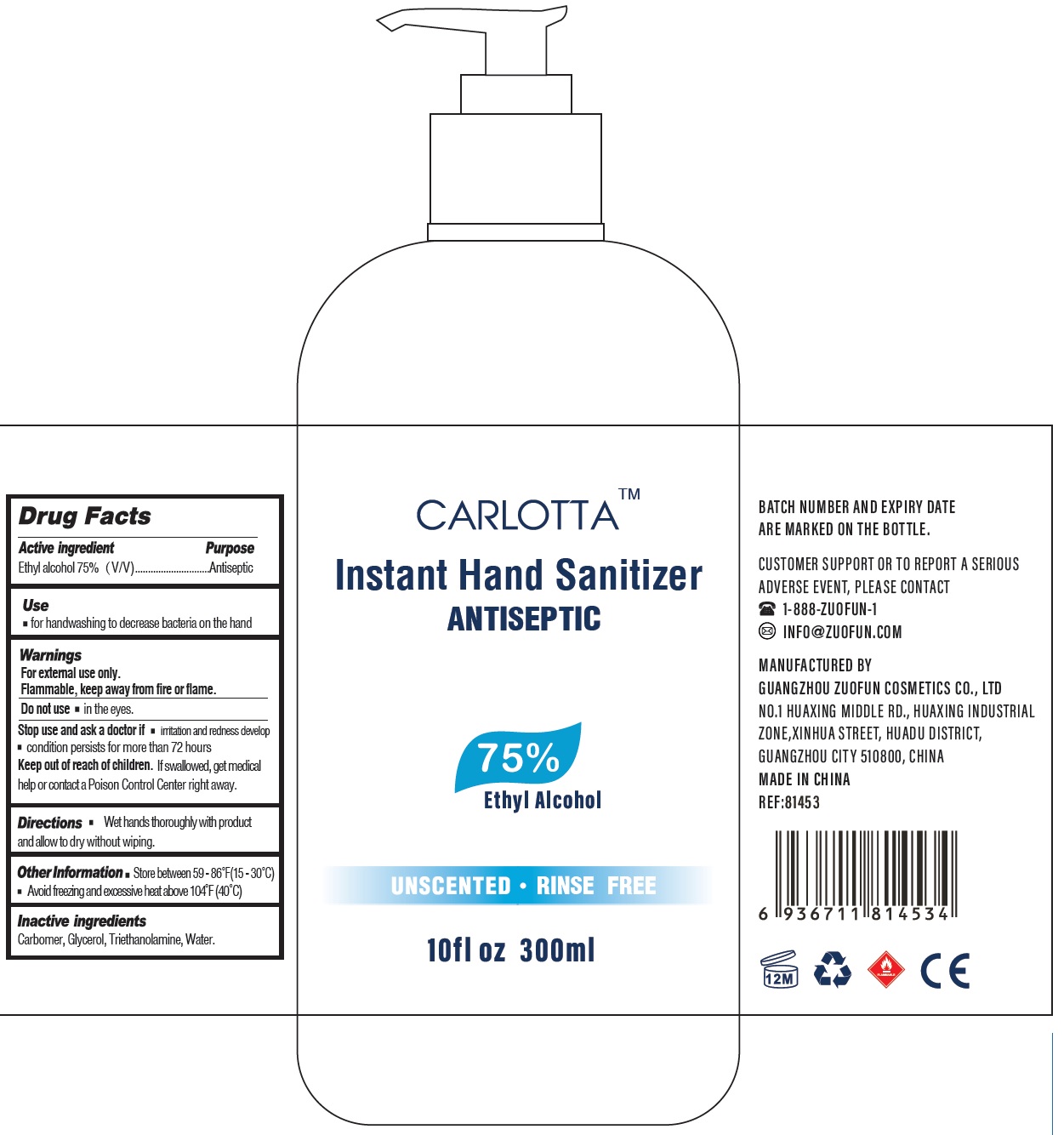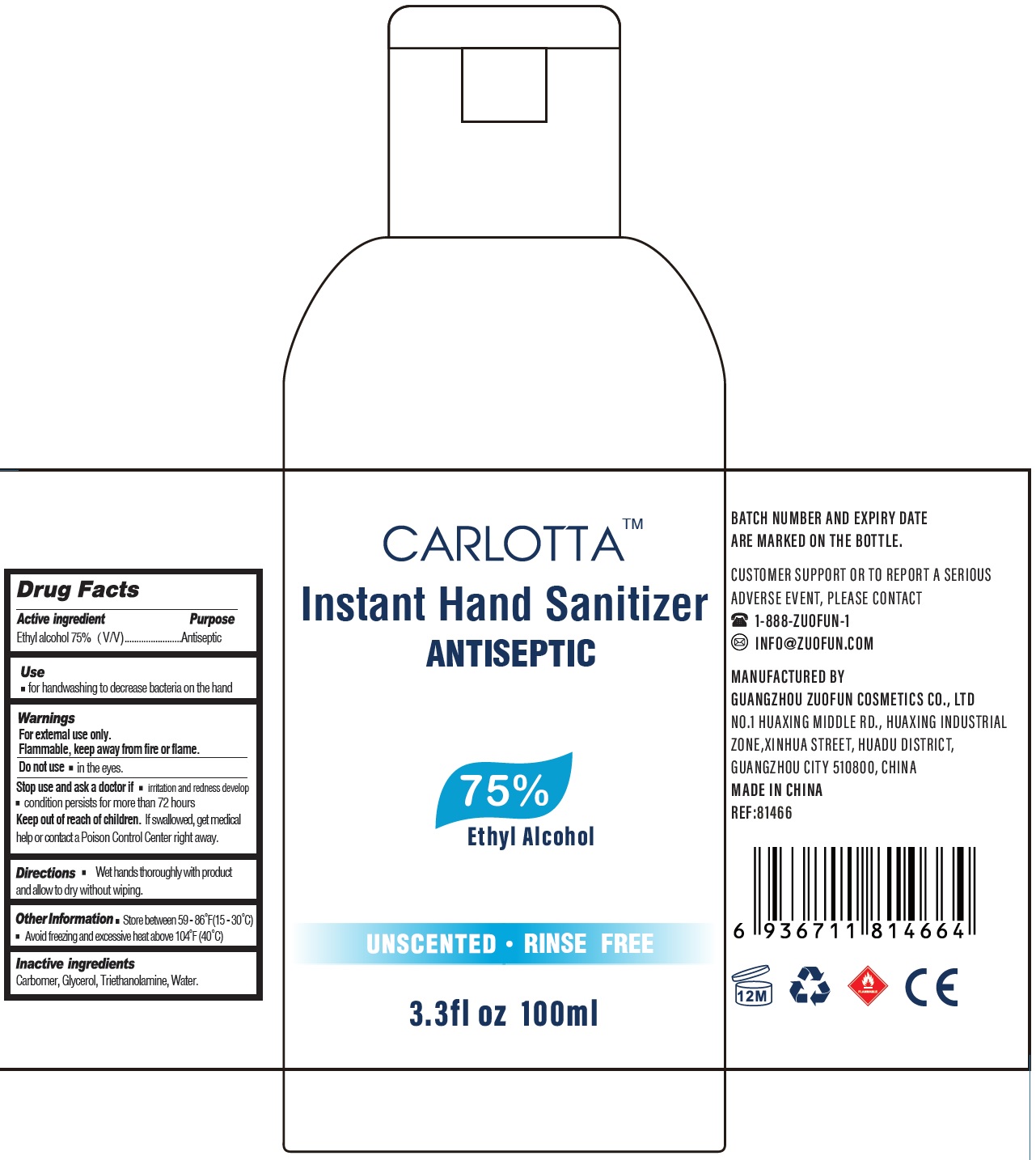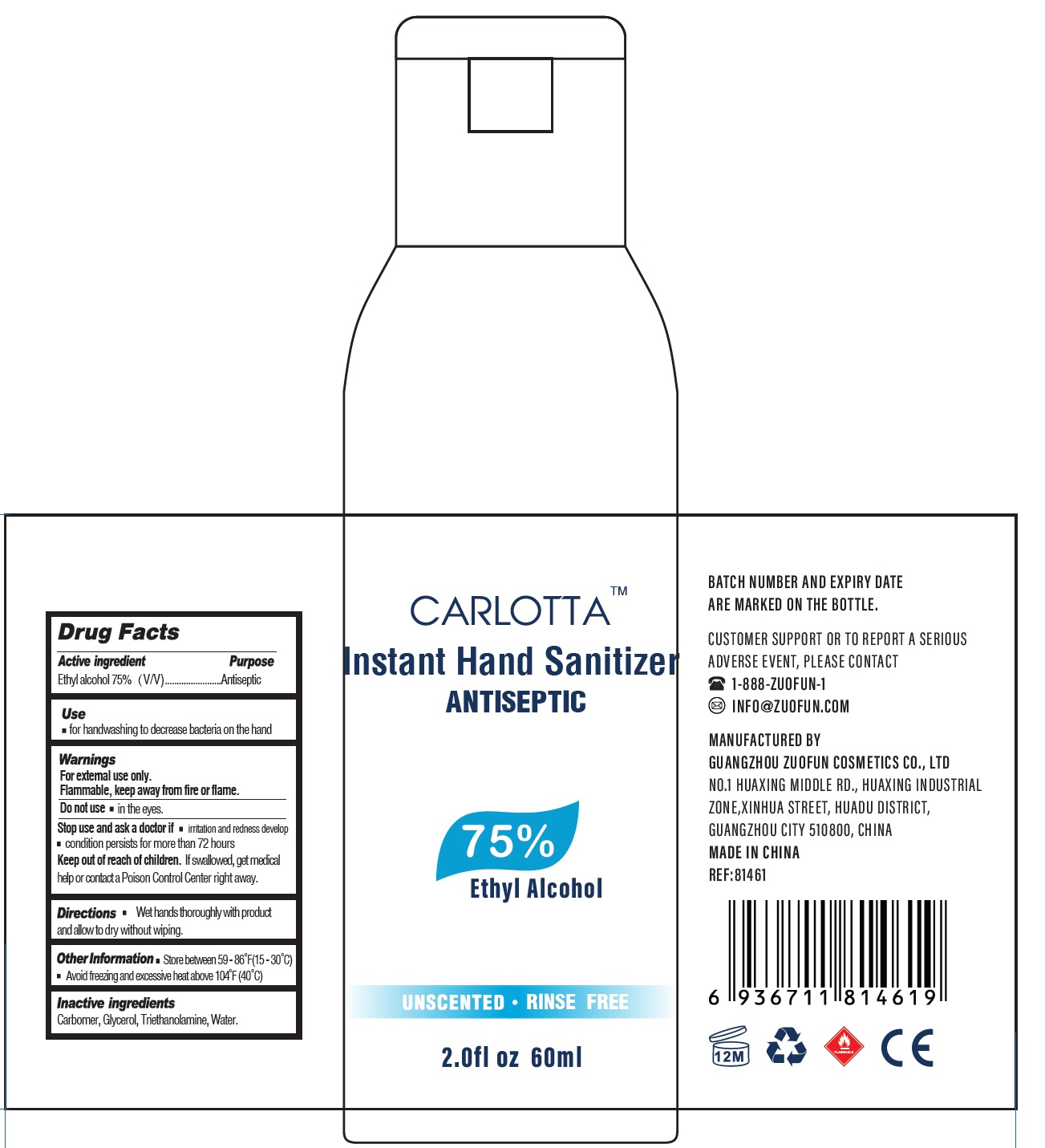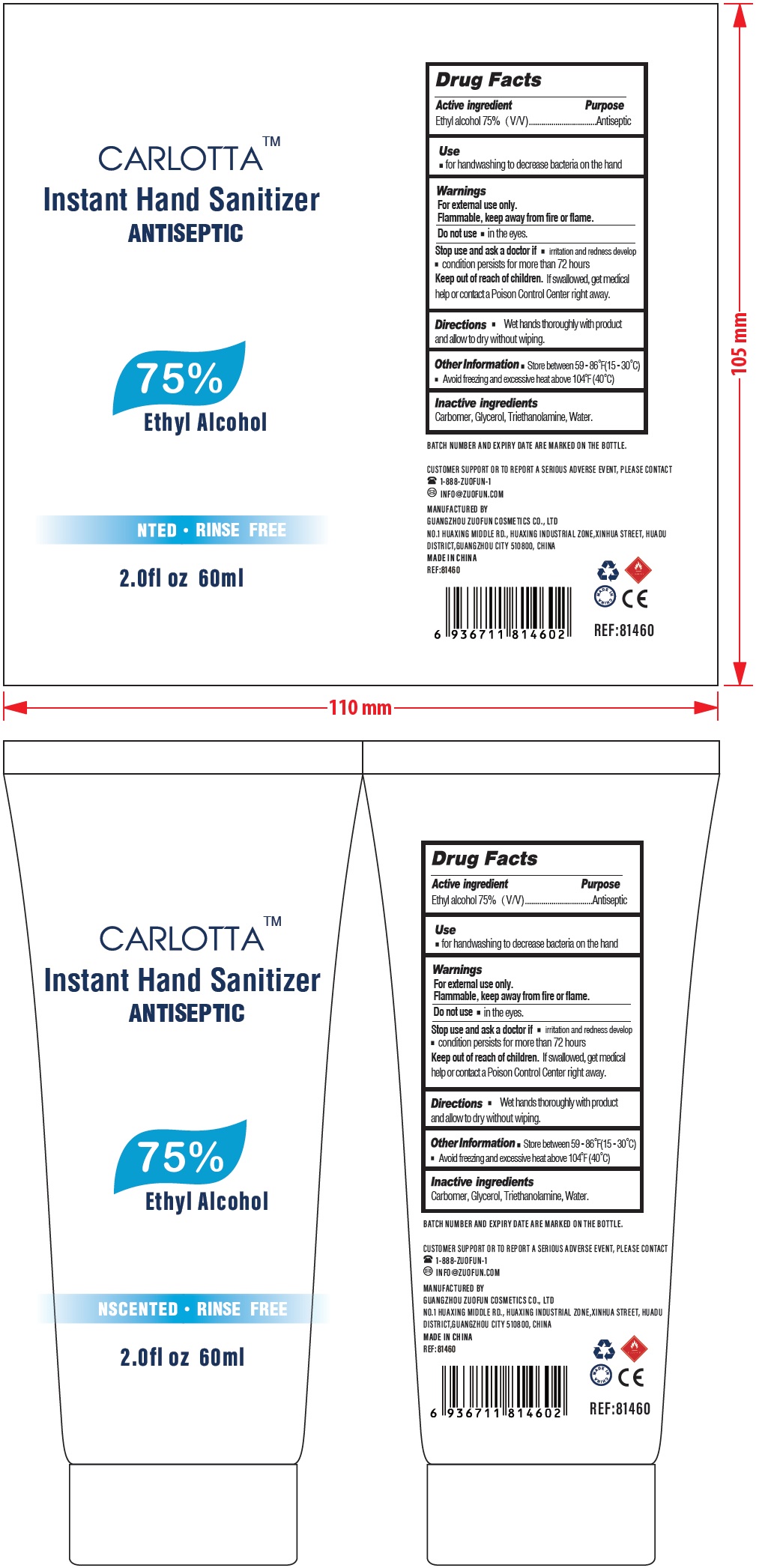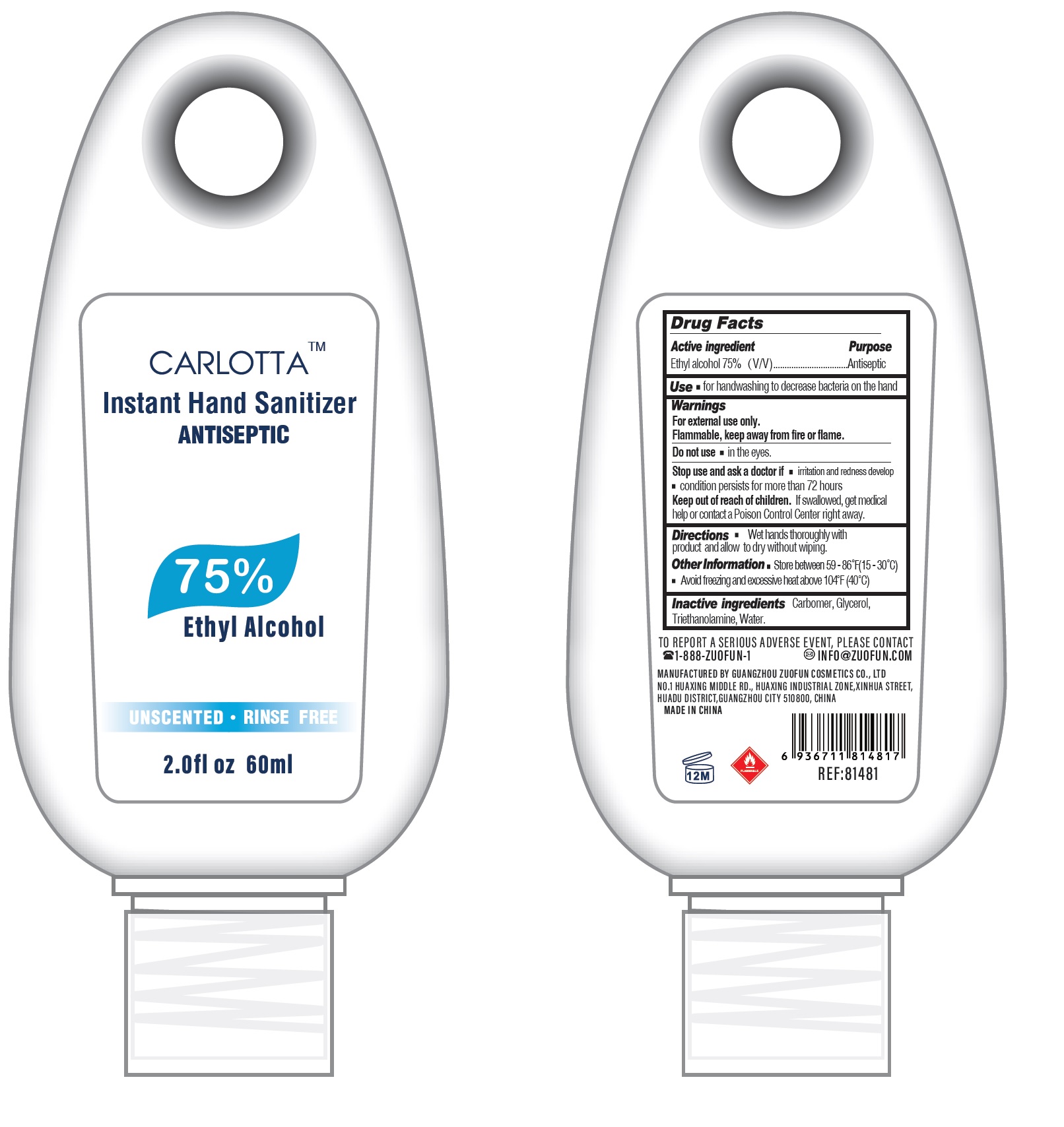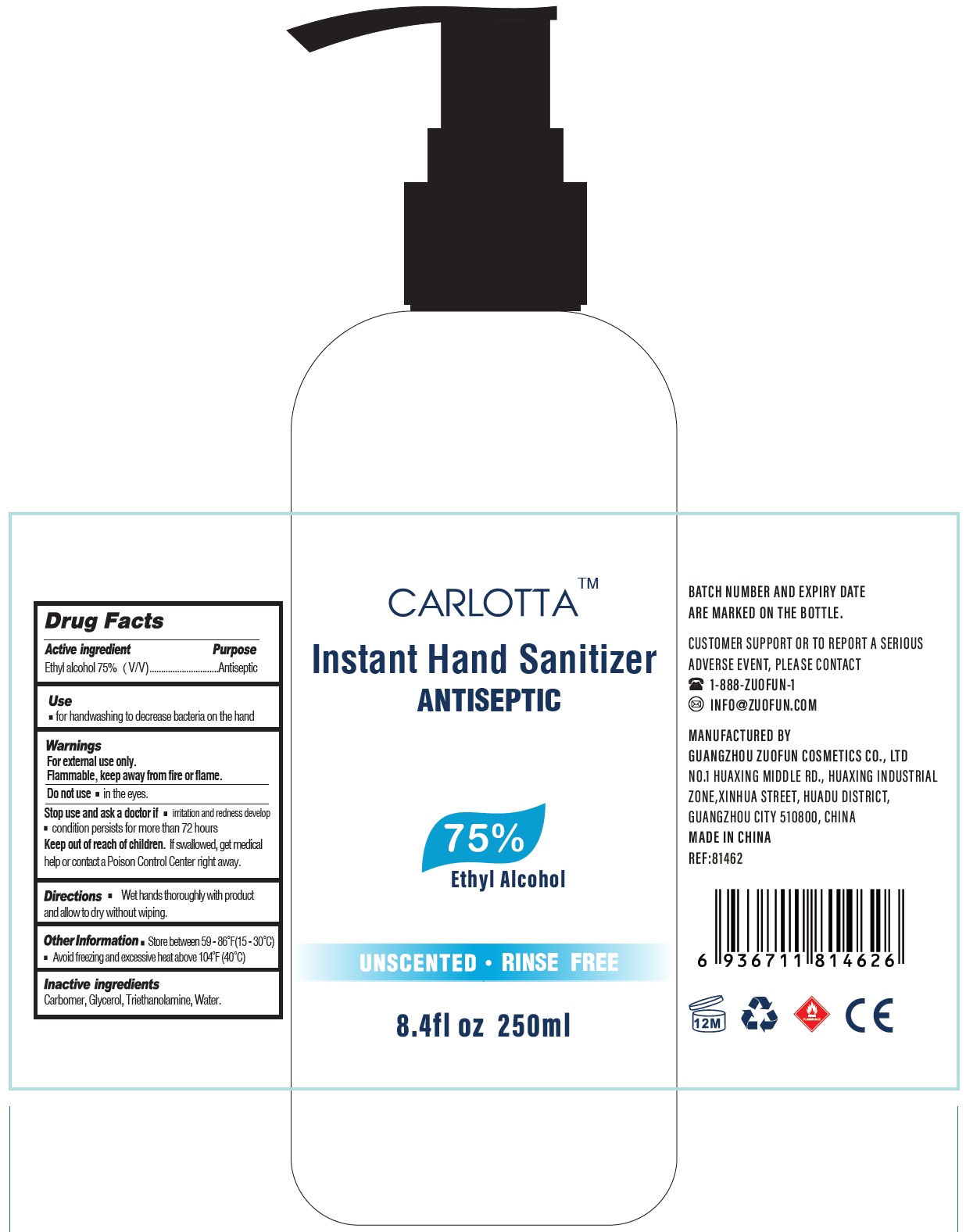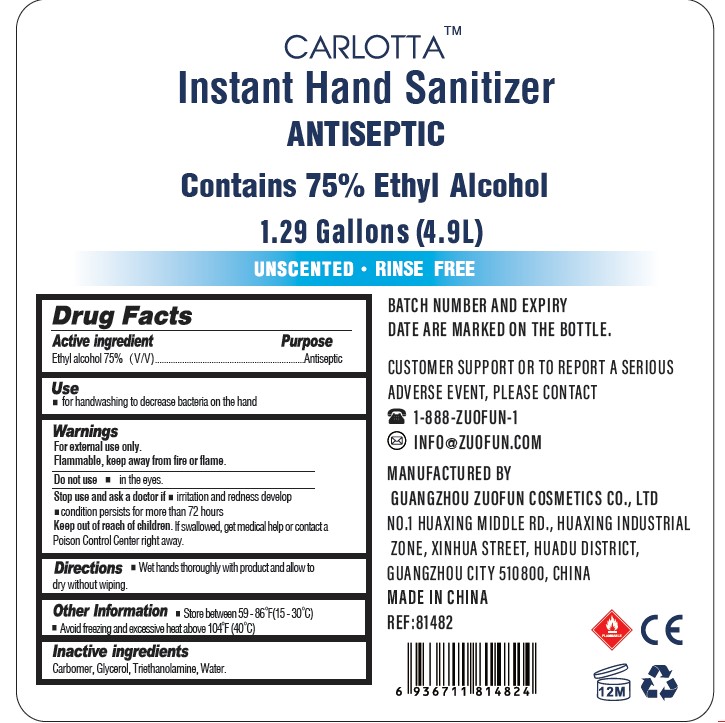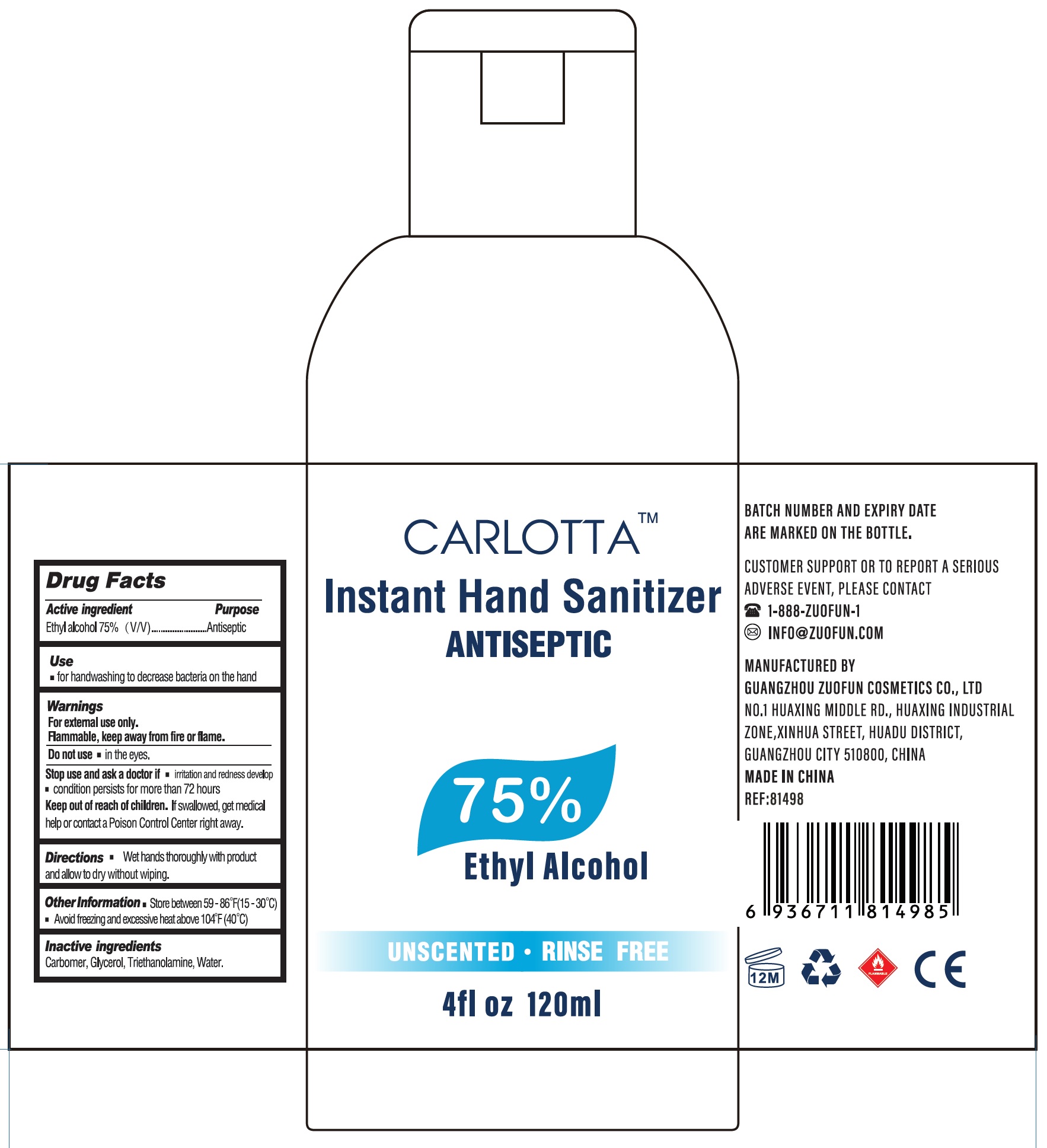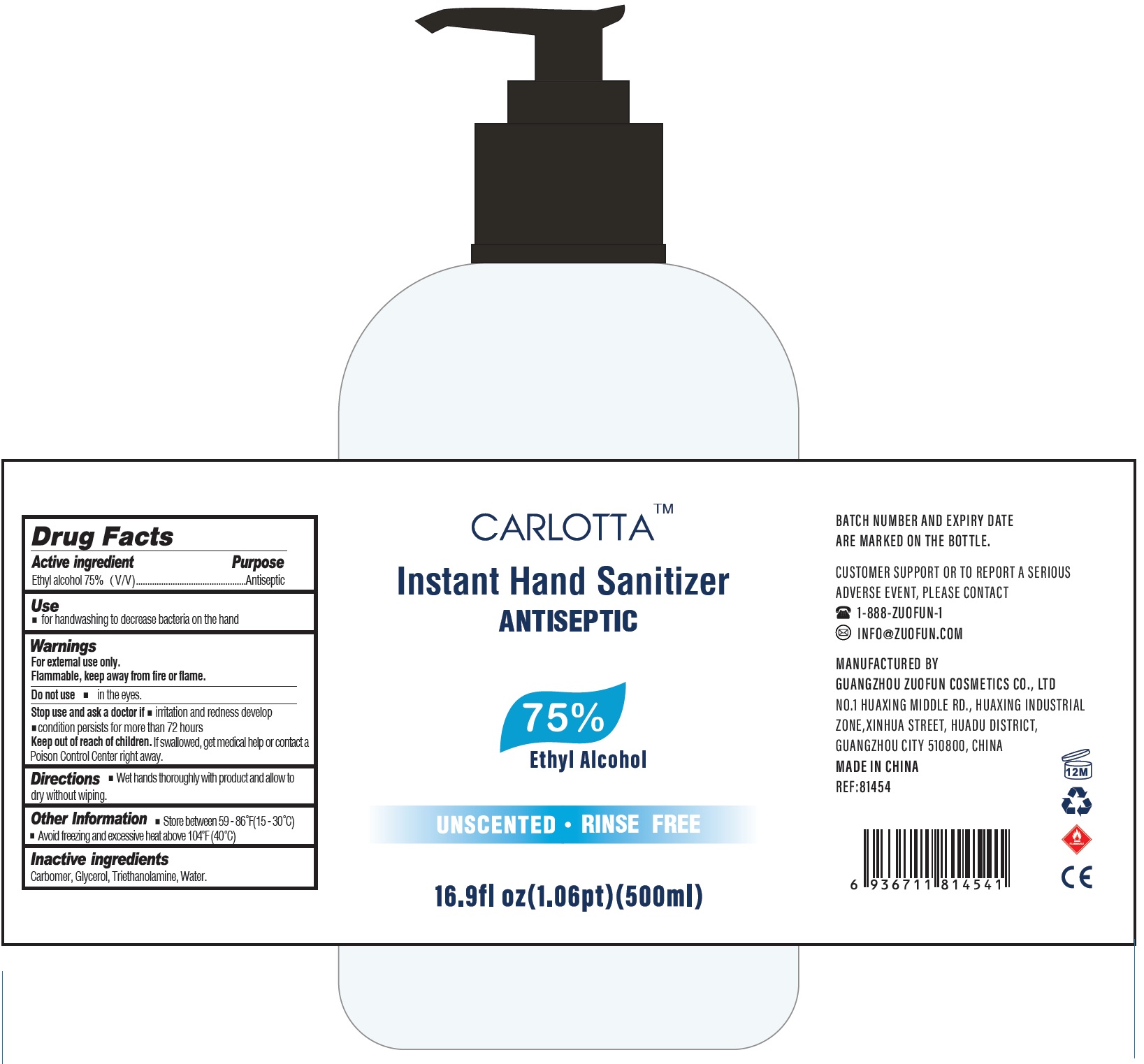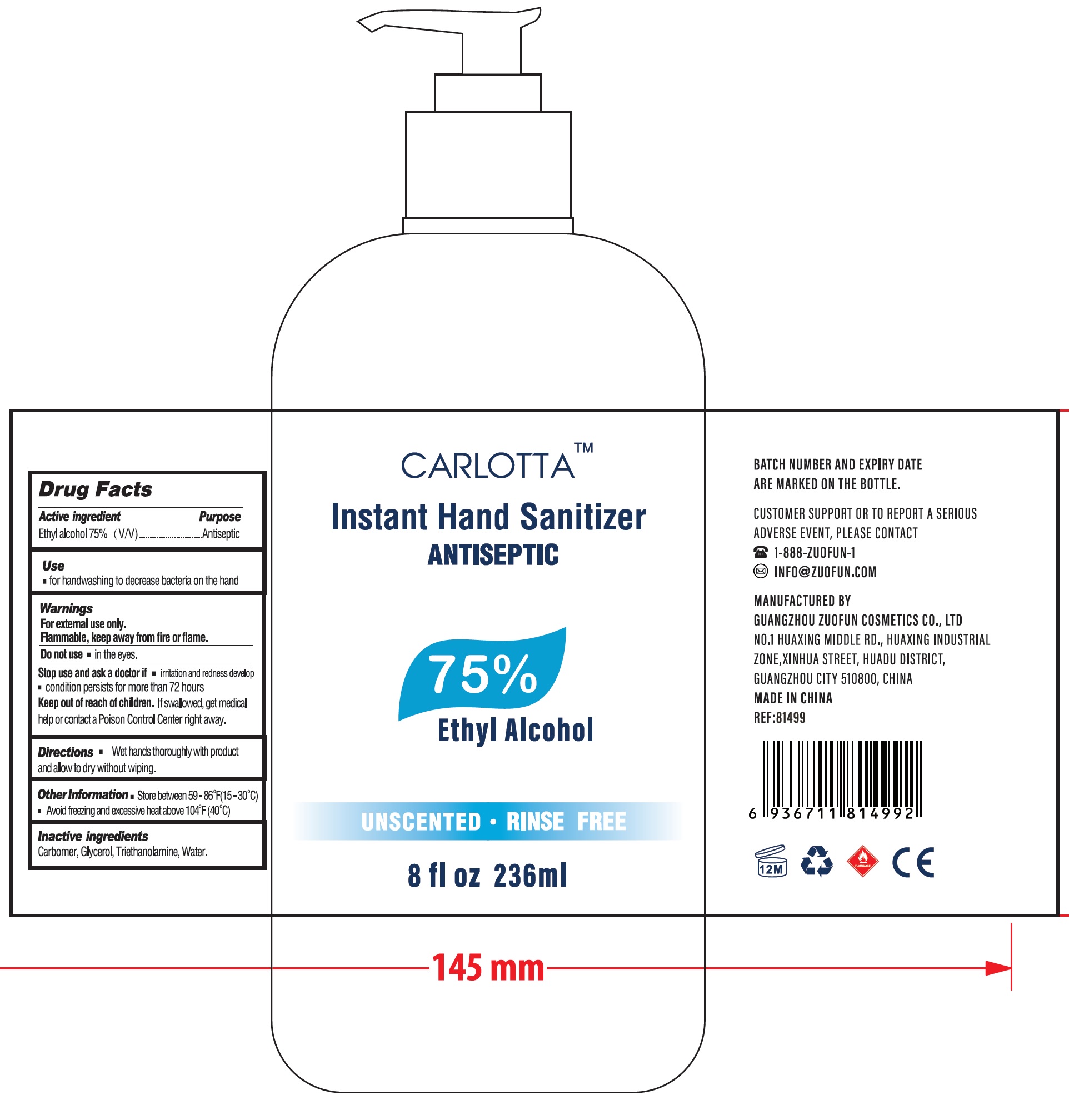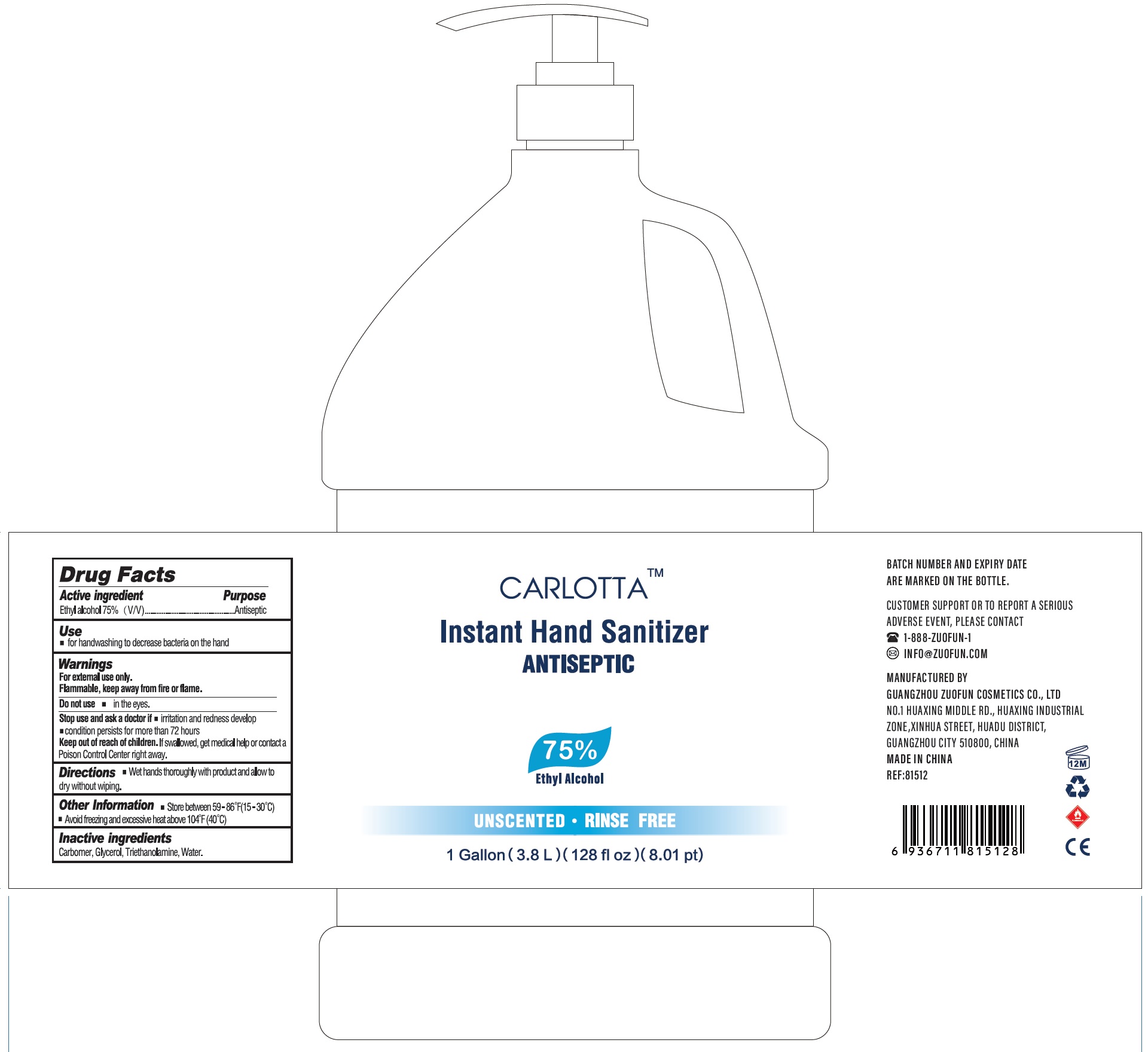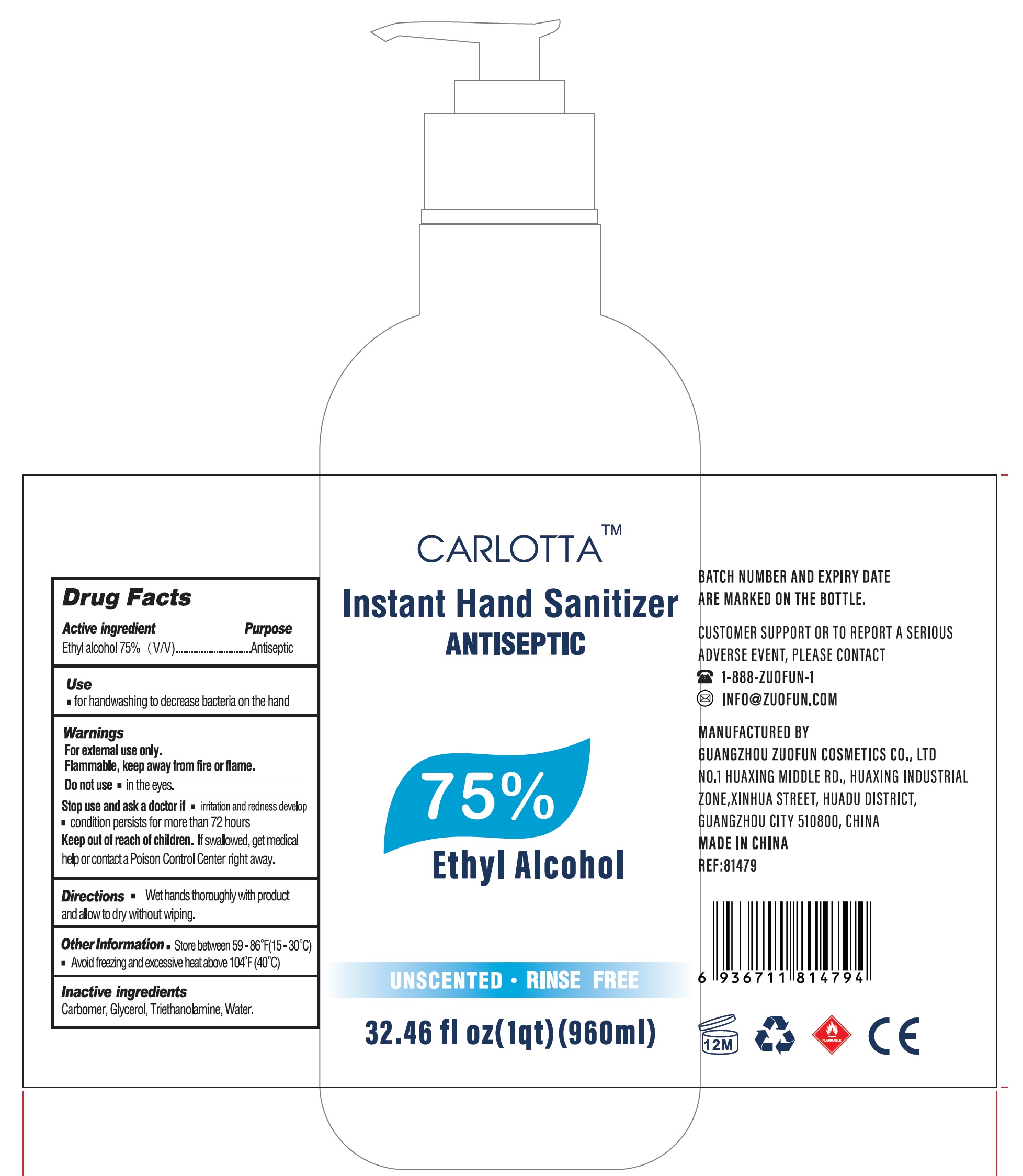 DRUG LABEL: Carlotta Instant Hand Sanitizer
NDC: 77027-000 | Form: GEL
Manufacturer: Guangzhou Zuofun Cosmetics Co., Ltd
Category: otc | Type: HUMAN OTC DRUG LABEL
Date: 20200728

ACTIVE INGREDIENTS: ALCOHOL 0.75 mL/1 mL
INACTIVE INGREDIENTS: CARBOMER HOMOPOLYMER, UNSPECIFIED TYPE; GLYCERIN; TROLAMINE; WATER

Carlotta Instant Hand Sanitizer

Active ingredient

Ethyl alcohol 75%（V/V)

Purpose

Antiseptic

Use

for handwashing to decrease bacteria on the hand

Warnings

For external use only..

Flammable, keep away from fire or flame.

Do not use

in the eyes.

Stop use and ask a doctor if

- irritation and redness develop
- condition persists for more than 72 hours

Keep out of reach of children.

If swallowed, get medical help or contact a Poison Control Center right away.

Directions

- Wet hands thoroughly with product and allow to

Other Information

- Store between 59-86°F (15-30°C)
- Avoid freezing and excessive heat above 104°F (40°C)

Inactive ingredients

Carbomer, Glycerol, Triethanolamine, Water.